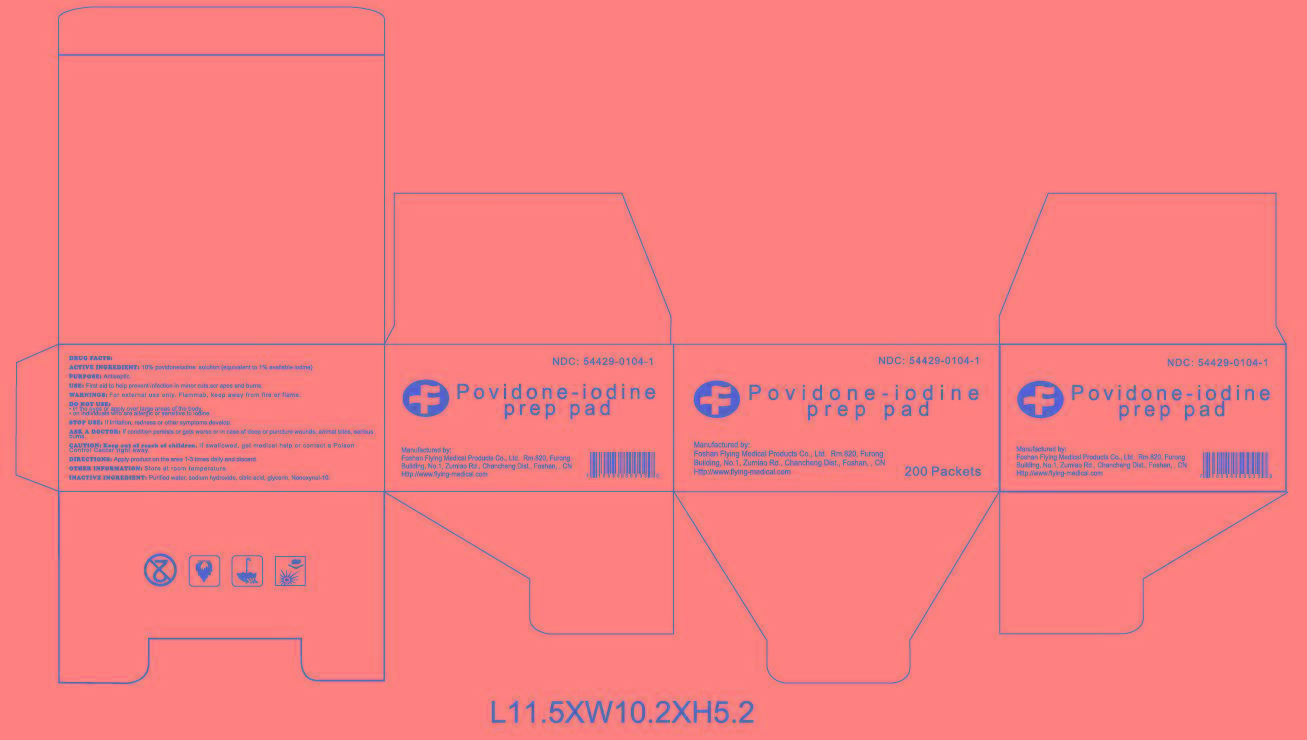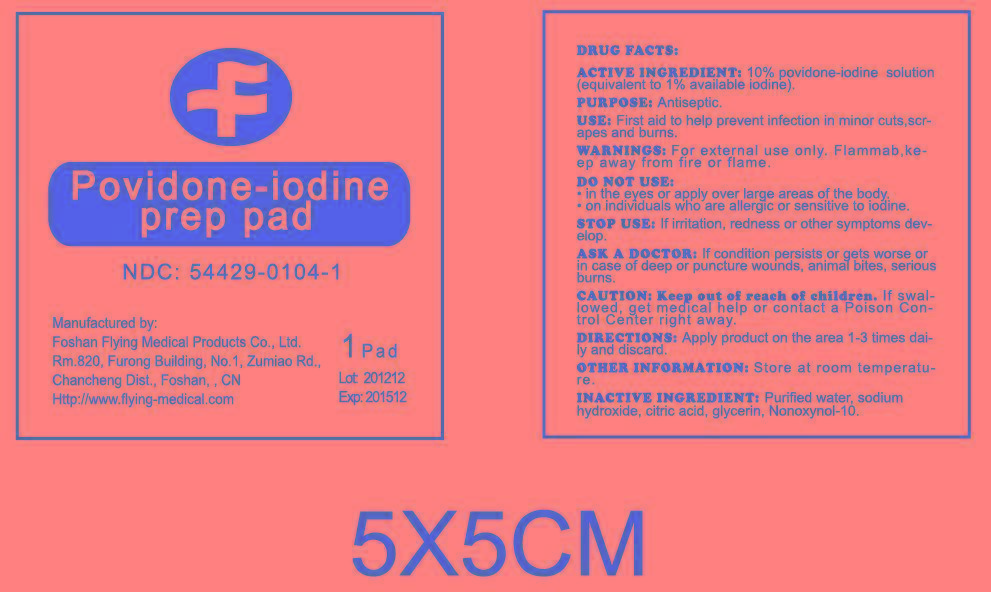 DRUG LABEL: Povidone-iodine prep pad
NDC: 54429-0104 | Form: SWAB
Manufacturer: Foshan Flying Medical Products Co., Ltd.
Category: otc | Type: HUMAN OTC DRUG LABEL
Date: 20181008

ACTIVE INGREDIENTS: POVIDONE-IODINE 9.43 g/100 g
INACTIVE INGREDIENTS: WATER; CITRIC ACID MONOHYDRATE; SODIUM HYDROXIDE

POVIDONE-IODINE PREP PAD

Active ingredient

Povidone Iodine USP, 10% w/v (equivalent to 1% titratable iodine)

Purpose

Antiseptic

CAUTION: Keep out of reach of children

If swallowed, get medical help or contact Poison Control Center right away.

Indications and usage section

First aid to help prevent infection in minor cuts, scrapes, and burns

WARNINGS

For external use only. Flammable, keep away from fire or flame.

Do notuse

﹒in the eyes or apply over large areas of the body.

﹒on individuals who are allergic or sensitive to iodine.

Stop use

If irritation, redness or other symptoms develop.

Ask a doctor

If condition persists or gets worse or in case of deep or puncture wounds, animal bites, serious burns.

Directions

Apply product on the area 1-3 times daily and discard.

INACTIVE INGREDIENT

ctric acid, glycerin, Nonoxynol-10, purified water, sodium hydroxide

DRUG FACTS

Active ingredient

Povidone Iodine USP, 10% w/v

(equivalent to 1% titratable iodine)

Purpose

Antiseptic

Use

First aid to help prevent infection in minor cuts, scrapes, and burns

Warnings

For external use only. Flammable, keep away from fire or flame.

Do notuse

﹒in the eyes or apply over large areas of the body.

﹒on individuals who are allergic or sensitive to iodine.

Stop use

If irritation, redness or other symptoms develop.

Ask a doctor

If condition persists or gets worse or in case of deep or puncture wounds, animal bites, serious burns.

CAUTION: Keep out of reach of children.

If swallowed, get medical help or contact Poison Control Center right away.

Directions

Apply product on the area 1-3 times daily and discard.

Other information: Store at room temperature.

Inactive ingredients

ctric acid, glycerin, Nonoxynol-10, purified water, sodium hydroxide